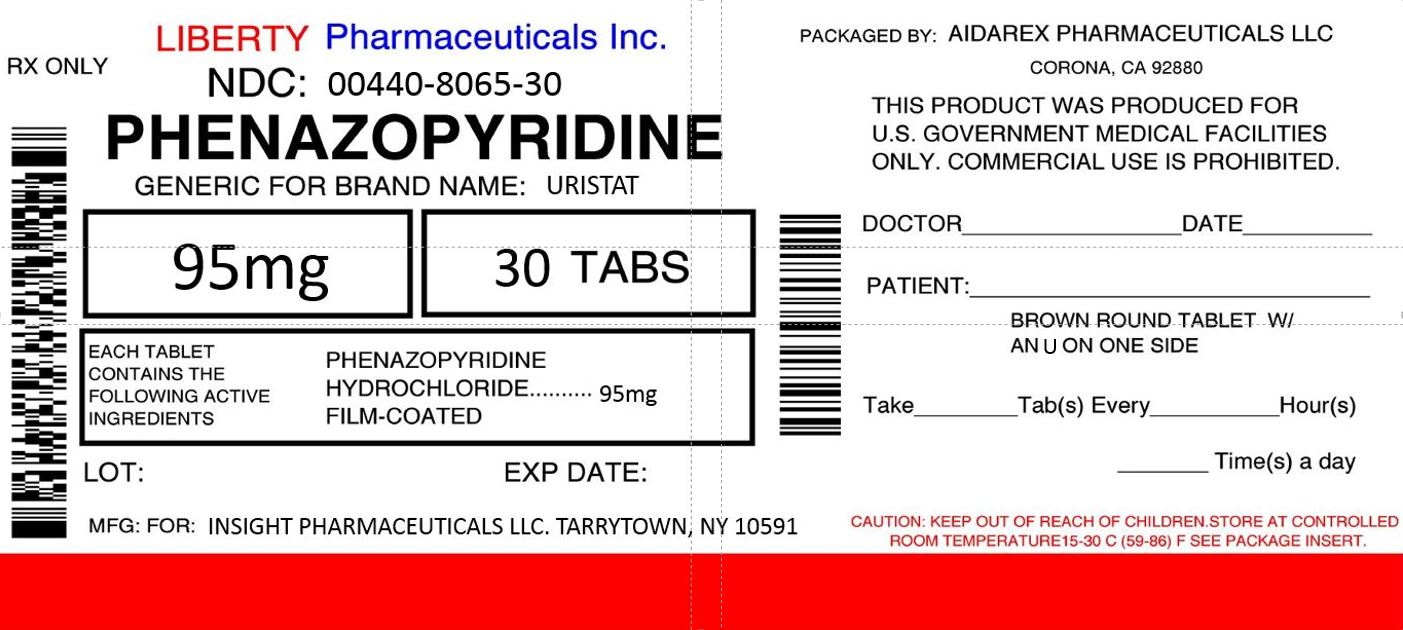 DRUG LABEL: UristatUTI Relief Pak
NDC: 0440-8065 | Form: TABLET
Manufacturer: Liberty Pharmaceuticals, Inc.
Category: otc | Type: HUMAN OTC DRUG LABEL
Date: 20161012

ACTIVE INGREDIENTS: PHENAZOPYRIDINE HYDROCHLORIDE 95 mg/1 1
INACTIVE INGREDIENTS: STARCH, CORN; CROSCARMELLOSE SODIUM; MAGNESIUM STEARATE; CELLULOSE, MICROCRYSTALLINE; SHELLAC

Uristat

Drug Facts

Active ingredient

(in each tablet)

Phenazopyridine hydrochloride 95mg

Purpose

Urinary analgesic

Use

fast relief from urinary pain, burning, urgency and frequency associated with urinary tract infections

Warnings

Do not exceed recommended dosage

Ask a doctor before use if you have

- Kidney disease
- Allergies to foods, preservatives, or dyes
- Had a hypersensitive reaction to phenazopyridine

When using this product

- Stomach upset may occur. Taking this product with or after meals may reduce stomach upset.
- Your urine will become reddish-orange in color. This is not harmful, but care should be taken to avoid staining clothing or other items.

Stop use and ask a doctor if

- Your symptoms last for more than 2 days
- You suspect you are having an adverse reaction to the medication

If pregnant or breast-feeding,

ask a health care professional before use.

Keep out of reach of children.

In case of an overdose, get medical help or contact a Poison Control Center (1-800-222-1222) right away.

Directions

- Adults and children 12 years of age and over: take 2 tablets 3 times daily with a full glass of water, with or after meals as needed.
- Children under 12 years of age: consult a doctor.
  Do not use for more than 2 days (12 tablets) without consulting a doctor

Other information

- This product may stain contact lenses
- This product can interfere with laboratory tests including urine, glucose (sugar), and ketones test
- Long term administration of phenazopyridine HCl has induced neoplasia in rats (large intestine) and mice (liver). Although no association between phenazopyridine hydrochloride and human neoplasia has been reported, adequate epidemiological studies along these lines have not been conducted
- Store at 20º-25º C (68º-77º F) in a dry place and protect from light.

Inactive ingredients

corn starch, croscarmellose sodium, magnesium stearate, microcrystalline cellulose, pharmaceutical glaze, polyvinylpyrrolidone, pregelatinized starch, silicon dioxide, and talc

Questions?

Call 1-800-344-7239 or visit our website at www.Uristat.com

©2015 Distributed by:
Insight Pharmaceuticals LLC
Tarrytown, NY 10591
A Prestige Brands Company

Repackaged By:

Aidarex Pharmaceuticals, LLC.

Corona, CA 92882

PRINCIPAL DISPLAY PANEL

Phenazopyridine Hydrochloride 95mg